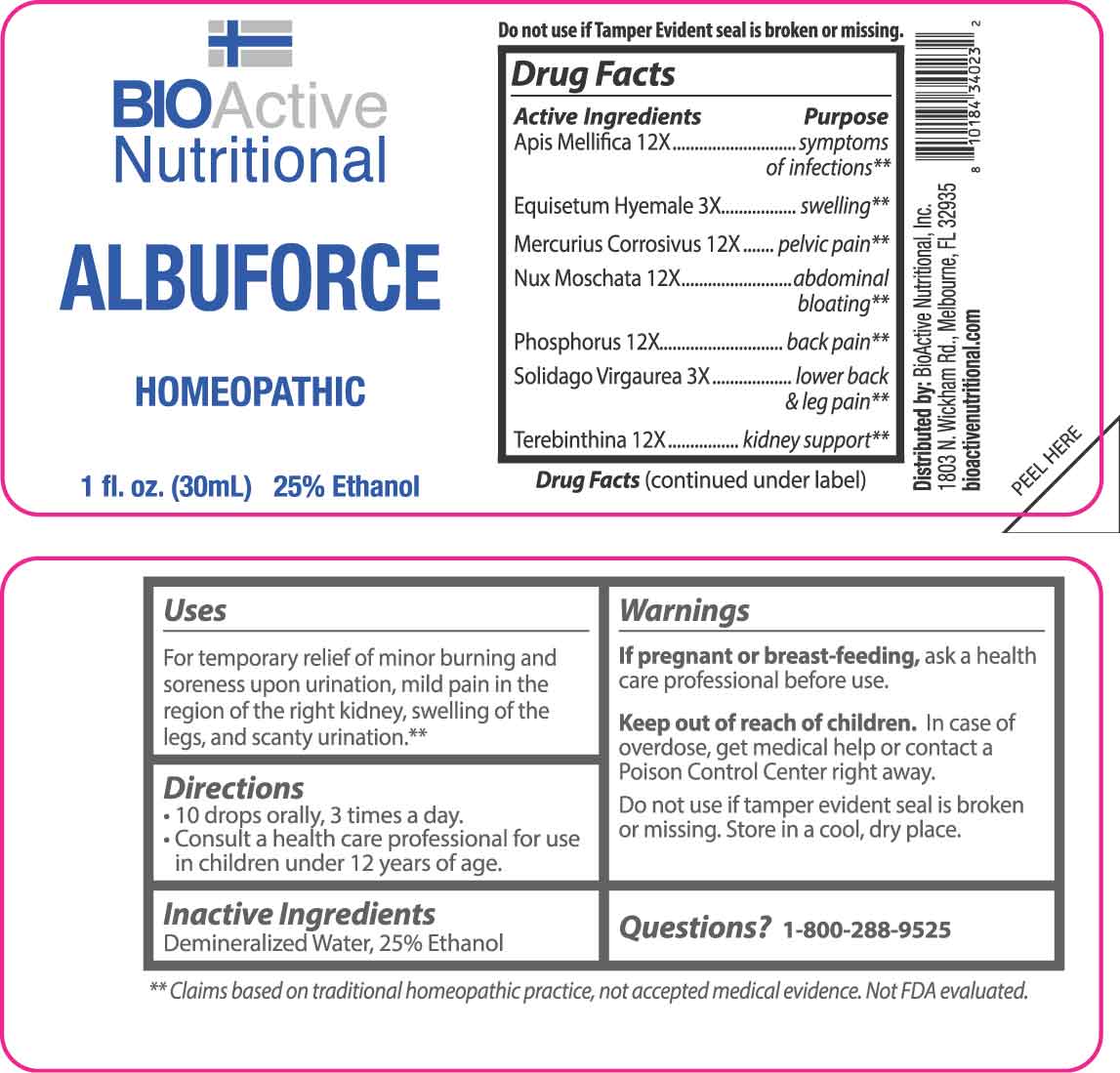 DRUG LABEL: Albuforce
NDC: 43857-0572 | Form: LIQUID
Manufacturer: BioActive Nutritional, Inc.
Category: homeopathic | Type: HUMAN OTC DRUG LABEL
Date: 20250519

ACTIVE INGREDIENTS: EQUISETUM HYEMALE WHOLE 3 [hp_X]/1 mL; SOLIDAGO VIRGAUREA FLOWERING TOP 3 [hp_X]/1 mL; APIS MELLIFERA 12 [hp_X]/1 mL; MERCURIC CHLORIDE 12 [hp_X]/1 mL; NUTMEG 12 [hp_X]/1 mL; PHOSPHORUS 12 [hp_X]/1 mL; TURPENTINE OIL 12 [hp_X]/1 mL
INACTIVE INGREDIENTS: WATER; ALCOHOL

DRUG FACTS:

ACTIVE INGREDIENTS:

Apis Mellifica 12X, Equisetum Hyemale 3X, Mercurius Corrosivus 12X, Nux Moschata 12X, Phosphorus 12X, Solidago Virgaurea 3X, Terebinthina 12X.

PURPOSE:

Apis Mellifica – symptoms of infections,** Equisetum Hyemale – swelling,** Mercurius Corrosivus – pelvic pain,** Nux Moschata – abdominal bloating,** Phosphorus – back pain,** Solidago Virgaurea – lower back & leg pain,** Terebinthina – kidney support**

**Claims based on traditional homeopathic practice, not accepted medical evidence. Not FDA evaluated.

USES:

For temporary relief of minor burning and soreness upon urination, mild pain in the region of the right kidney, swelling of the legs, and scanty urination.**

**Claims based on traditional homeopathic practice, not accepted medical evidence. Not FDA evaluated.

WARNINGS:

If pregnant or breast-feeding, ask a health care professional before use.

Keep out of reach of children. In case of overdose, get medical help or contact a Poison Control Center right away.

Do not use if tamper evident seal is broken or missing.

Store in a cool, dry place.

KEEP OUT OF REACH OF CHILDREN:

In case of overdose, get medical help or contact a Poison Control Center right away.

DIRECTIONS:

• 10 drops orally, 3 times a day.

• Consult a health care professional for use in children under 12 years of age.

QUESTIONS:

Demineralized Water, 25% Ethanol

QUESTIONS:

Distributed by:
BioActive Nutritional, Inc.
1803 N. Wickham Rd.
Melbourne, FL 32935
bioactivenutritional.com

1-800-288-9525

PACKAGE LABEL DISPLAY

BIOActive Nutritional

ALBUFORCE

HOMEOPATHIC

1 FL OZ (30 ml)